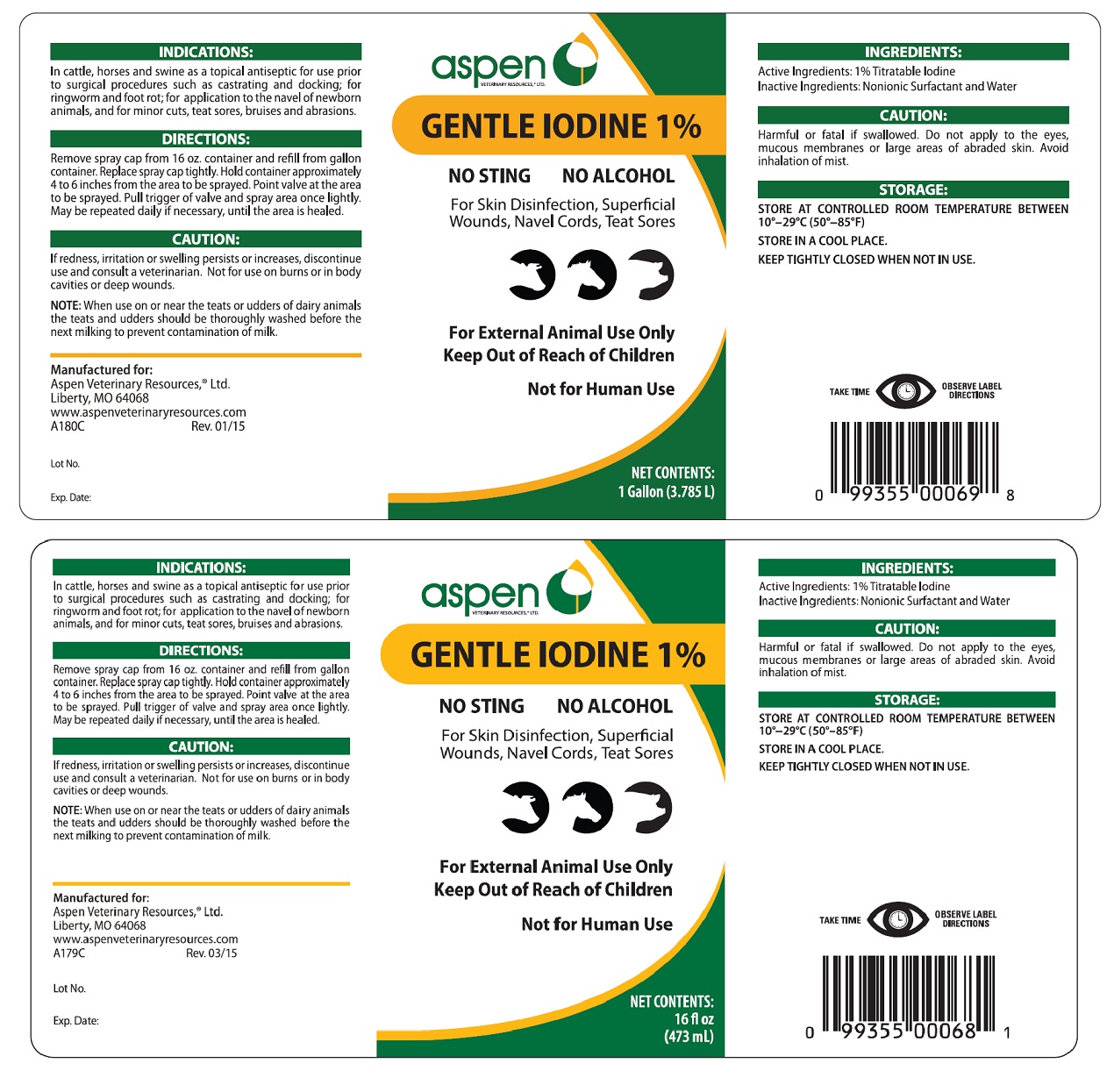 DRUG LABEL: Gentle Iodine 1%
NDC: 46066-031 | Form: SOLUTION
Manufacturer: Aspen Veterinary Resources Ltd
Category: animal | Type: OTC ANIMAL DRUG LABEL
Date: 20241121

ACTIVE INGREDIENTS: IODINE 0.01 mg/1 mL
INACTIVE INGREDIENTS: WATER 0.99 mg/1 mL

WARNINGS AND PRECAUTIONS

Gentle Iodine 1%

No Sting

No Alcohol

For Skin Disinfection, Superficial Wounds, Navel Cords, Teat Sores

For External Animal Use Only

Keep Out of Reach of Children

Not for Human Use

INDICATIONS

In cattle, horses, and swine as a topical antiseptic for use prior to surgical procedures such as castrating and docking; for ringworm and foot rot; for application to the navel of newborn animals; and for minor cuts, teat sores, bruises, and abrasions.

DIRECTIONS

Remove spray cap from 16 oz. container and refill from gallon container. Replace spray cap tightly. Hold container approximately 4 to 6 inches from the area to be sprayed. Point valve at the area to be sprayed. Pull trigger of valve and spray area once lightly. May be repeated daily if necessary, until the area is healed.

CAUTION

If redness, irritation, or swelling persists or increases discontinue use and consult a veterinarian. Not for use on burns or in body cavities or deep wounds.

NOTE

When used on or near the teats or udders of dairy animals, the teats and udders should be thoroughly washed before the next milking to prevent contamination of milk.

INGREDIENTS

Active Ingredients: 1% Titratable Iodine

Inactive Ingredients: Nonionic Surfactant and Water

CAUTION

Harmful or fatal if swallowed. Do not apply to the eyes, mucous membranes or large areas of abraded skin. Avoi inhalation of mist.

STORAGE

STORE AT CONTROLLED ROOM TEMPERATURE BETWEEN 10°-29°C (50°-85°F)

STORE IN A COOL PLACE

KEEP TIGHTLY CLOSED WHEN NOT IN USE.

Manufactured for:

Aspen Veterinary Resources®, Ltd.

Liberty, MO 64068

www.aspenveterinaryresources.com